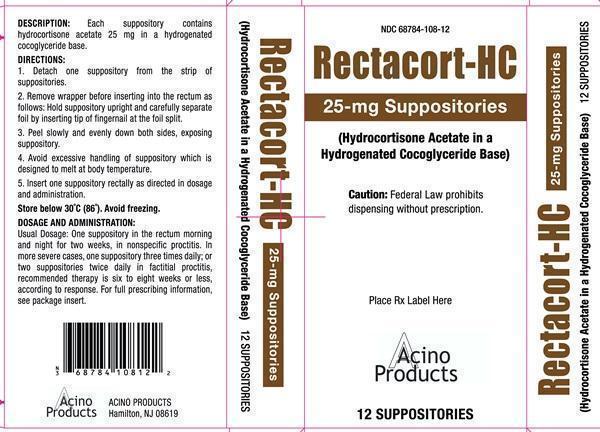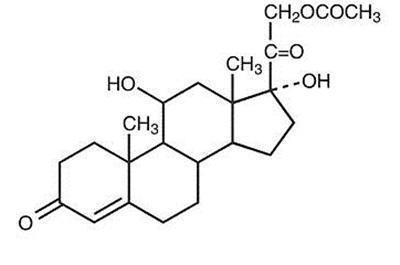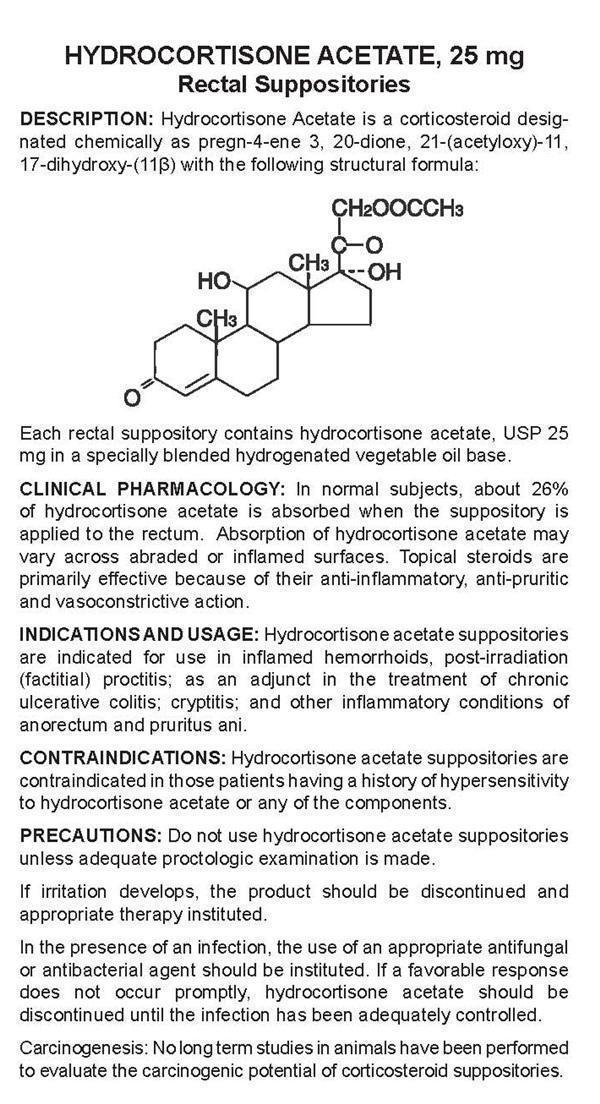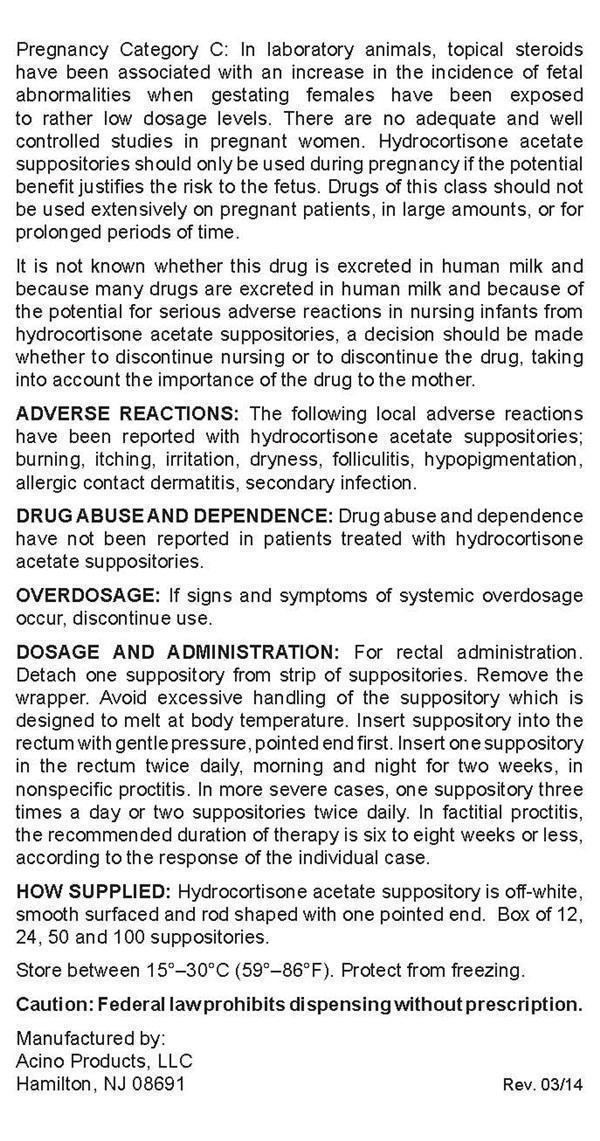 DRUG LABEL: Rectacort - HC
NDC: 68784-108 | Form: SUPPOSITORY
Manufacturer: Acino Products, LLC.
Category: prescription | Type: HUMAN PRESCRIPTION DRUG LABEL
Date: 20140619

ACTIVE INGREDIENTS: HYDROCORTISONE ACETATE 25 mg/1 1
INACTIVE INGREDIENTS: HYDROGENATED COCO-GLYCERIDES

DESCRIPTION:

HYDROCORTISONE ACETATE, 25 mg
Rectal Suppositories
DESCRIPTION: Hydrocortisone Acetate is a corticosteroid designated chemically as pregn-4-ene-3, 20-dione, 21-(acetyloxy)-11, 17-dihydroxy-(11β) with the following structural formula:

Each rectal suppository contains hydrocortisone acetate, USP 25 mg in a specially blended hydrogenated vegetable oil base.

CLINICAL PHARMACOLOGY:

In normal subjects, about 26% of hydrocortisone acetate is absorbed when the suppository is applied to the rectum. Absorption of hydrocortisone acetate may vary across abraded or inflamed surfaces. Topical steroids are primarily effective because of their anti-inflammatory, anti-pruritic and vasconstrictive action.

INDICATIONS AND USAGE:

Hydrocortisone acetate suppositories are indicated for the use in inflamed hemorrhoids, post-irradiation (factitial) proctitis; as an adjunct in the treatment of chronic ulcerative colitis; cryptitis; and other inflammatory conditions of anorectum and puritus ani.

CONTRAINDICATIONS:

Hydrocortisone acetate suppositories are indicated for use in inflamed hemorrhoids, post-irradiation (factitial) proctitis; as an adjunct in the treatment of chronic ulcerative colitis; cryptitis; and other inflammatory conditions of anorectum and pruritus ani.

PRECAUTIONS:

Do not use hydrocortisone acetate suppositories unless a adequate proctologic examination is made.
If irritation develops, the product should be discontinued and appropriate therapy instituted.
In the presence of an infection, the use of an appropriate antifungal or antibacterial agent should be instituted. If a favorable response does not occur promptly, hydrocortisone acetate should be discontinued until the infection has been adequately controlled.
Carcinogenesis: No long term studies in animals have been performed to evaluate the carcinogenic potential of corticosteroid suppositories.
Pregnancy Category C: In laboratory animals, topical steroids have been associated with an increase in the incidence of fetal abnormalities when gestating females have been exposed to rather low dosage levels. There are no adequate and well controlled studies in pregnant women. Hydrocortisone acetate suppositories should only be used during pregnancy if the potential benefit justifies the risk to the fetus. Drugs of this class should not be used extensively on pregnant patients, in large amounts, or for prolonged periods of time.
It is not known whether this drug is excreted in human milk and because many drugs are excreted in human milk and because of the potential for serious adverse reactions in nursing infants from hydrocortisone acetate suppositories, a decision should be made whether to discontinue nursing or to discontinue the drug, taking into account the importance of the drug to the mother.

ADVERSE REACTIONS:

The following local adverse reactions have been reported with hydrocortisone acetate suppositories; burning, itching, irritation, dryness, folliculitis, hypopigmentation, allergic contact dermatitis, secondary infection.

Drug abuse and dependence have not been reported in patients treated with hydrocortisone acetate suppositories.

OVERDOSAGE:

If signs and symptoms of systemic overdosage occur, discontinue use.

DOSAGE AND ADMINISTRATION:

For rectal administration. Detach one suppository from strip of suppositories. Remove the wrapper. Avoid excessive handling of the suppository which is designed to melt at body temperature. Insert suppository into the rectum with gentle pressure, pointed end first. Insert one suppository in the rectum twice daily, morning and night for two weeks, in nonspecific proctitis. In more severe cases, one suppository three times a day or two suppositories twice daily. In factitial proctitis, the recommended duration of therapy is six to eight weeks or less, according to the response of the individual case.

HOW SUPPLIED:

Hydrocortisone acetate suppository is off-white, smooth surfaced and rod shaped with one pointed end. Box of 12, 24, 50, 100 suppositories.
Store between 15°-30°C(59°-86°F). Protect from freezing

Rectacort-HC Product Label

NDC 68784-108-12
Rectacort - HC
25-mg Suppositories
(Hydrocortisone Acetate in a Hydrogenated Cocoglyceride Base)
Caution: Federal Law prohibits dispensing without prescription.
Place Rx Label Here
Acino Products
12 SUPPOSITORIES
DESCRIPTION: Each suppository contains hydrocortisone acetate 25 mg in a hydrogenated cocoglyceride base.
DIRECTIONS:
1. Detach one suppository from the strip of suppositories.
2. Remove wrapper before inserting into the rectum as follows: Hold suppository upright and carefully separate foil by inserting tip of fingernail at the foil split.
3. Peel slowly and evenly down both sides, exposing suppository.
4. Avoid excessive handling of suppository which is designed to melt at body temperature.
5. Insert one suppository rectally as directed in dosage and administration.
Store below 30°C (86°F). Avoid freezing
DOSAGE AND ADMINISTRATION:
Usual Dosage: One suppository in the rectum morning and night for two weeks, in nonspecific procititis. In more severe cases, one suppository three times daily; or two suppositories twice daily in factitial proctitis, recommended therapy is six to eight weeks or less, according to response. For full prescribing information, see packet insert.
ACINO PRODUCTS Hamilton, NJ 08619

Rectacort - HC Package Insert

HYDROCORTISONE ACETATE, 25 mg
Rectal Suppositories
Manufactured by:
Acino Products, LLC
Hamilton, NJ 08691 Rev. 03/14